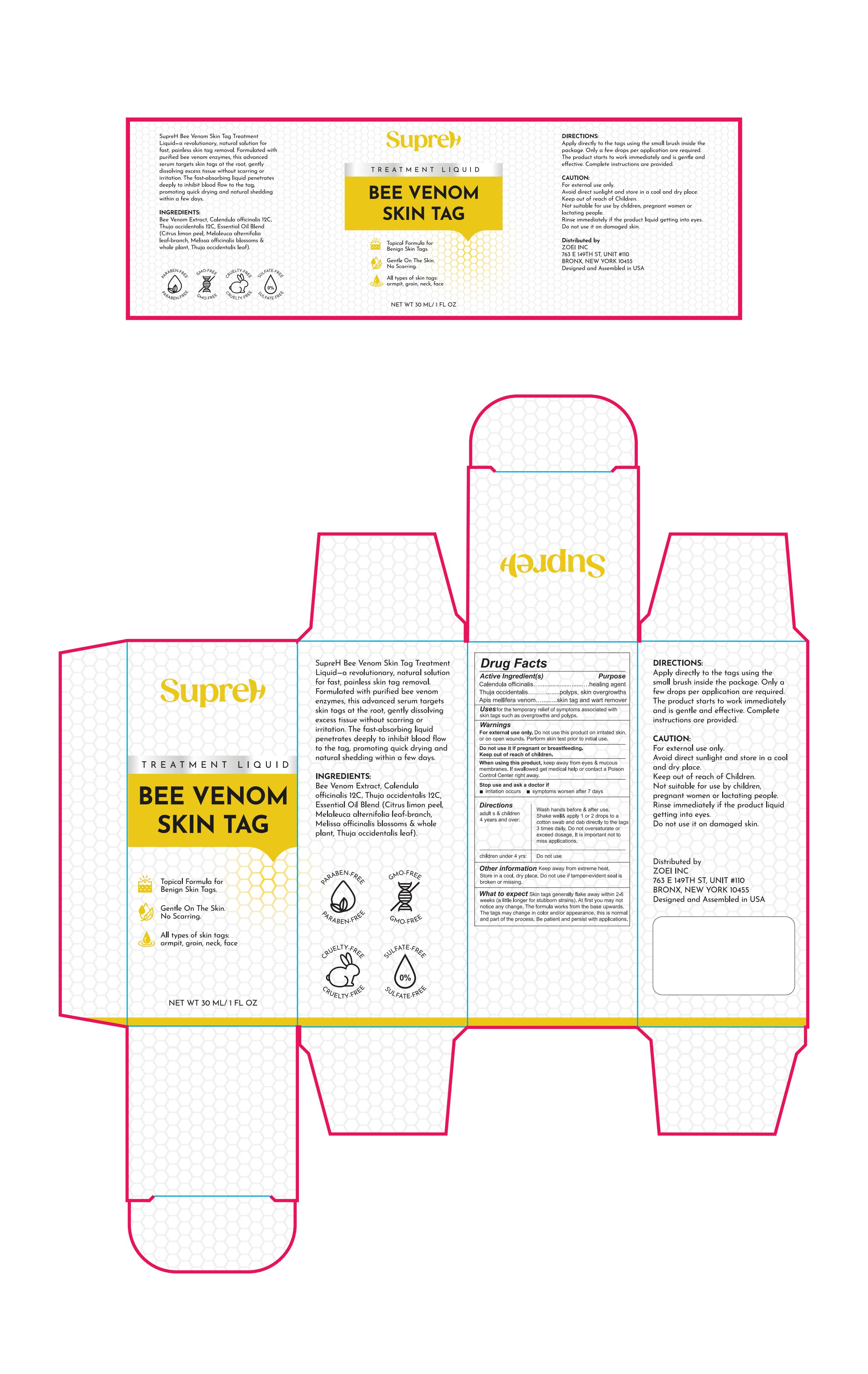 DRUG LABEL: SupreH Bee Venom Skin Tag Treatment Liquid
NDC: 83818-012 | Form: LIQUID
Manufacturer: Shenzhen Xinxin Yunhai Technology Co., Ltd.
Category: otc | Type: HUMAN OTC DRUG LABEL
Date: 20250523

ACTIVE INGREDIENTS: THUJA OCCIDENTALIS WHOLE 2 g/100 mL; APIS MELLIFERA VENOM 2 g/100 mL; CALENDULA OFFICINALIS FLOWER 2 g/100 mL
INACTIVE INGREDIENTS: PHELLODENDRON CHINENSE WHOLE; MELISSA OFFICINALIS WHOLE; SALICYLIC ACID; CITRUS LIMON (LEMON) PEEL OIL; MELALEUCA ALTERNIFOLIA (TEA TREE) LEAF OIL; PRUNUS AMYGDALUS DULCIS (SWEET ALMOND) OIL

83818-012

Active Ingredient

Calendula officinalis 2%

Thuja occidentalis 2%

Apis mellifera venom 2%

Purpose

Calendula officinalis ……healing agent
Thuja occidentalis………polyps, skin overgrowths
Apis mellifera venom……skin tag and wart remover

Use

for the temporary relief of symptoms associated with skin tags such as overgrowths and polyps

Warnings

For external use only. Do not use this product on irritated skin, or on open wounds. Perform skin test prior to initial use.

Do not use it if pregnant or breastfeeding. Keep out of reach of children.

When Using

When using this product, keep away from eyes & mucous membranes. If swallowed get medical help or contact a Poison Control Center right away.

Stop Use

Stop use and ask a doctor if
1.Irritation occurs
2.symptoms worsen after 7 days

Ask Doctor

Stop use and ask a doctor if
1.Irritation occurs
2.symptoms worsen after 7 days

Keep Out Of Reach Of Children

Please keep out of reach of children. If children accidentally swallow it, please call the emergency center immediately.

Directions

Adult s & children 4 years and over:
Wash hands before & after use. Shake well& apply 1 or 2 drops to a cotton swab and dab directly to the tags 3 times daily. Do not oversaturate or exceed dosage. It is important not to miss applications.

Children under 4 yrs: Do not use

Other information

Keep away from extreme heat. Store in a cool, dry place. Do not use if tamper-evident seal is broken or missing.

Inactive ingredients

PHELLODENDRON CHINENSIS WHOLE
CITRUS LIMON (LEMON) PEEL OIL
MELALEUCA ALTERNIFOLIA (TEA TREE) LEAF OIL
MELISSA OFFICINALIS WHOLE
SWEET ALMOND OIL
SALICYLIC ACID

What to expect

Skin tags generally flake away within 2-6 weeks (a little longer for stubborn strains). At first you may not notice any change. The formula works from the base upwards. The tags may change in color and/or appearance, this is normal and part of the process. Be patient and persist with applications.